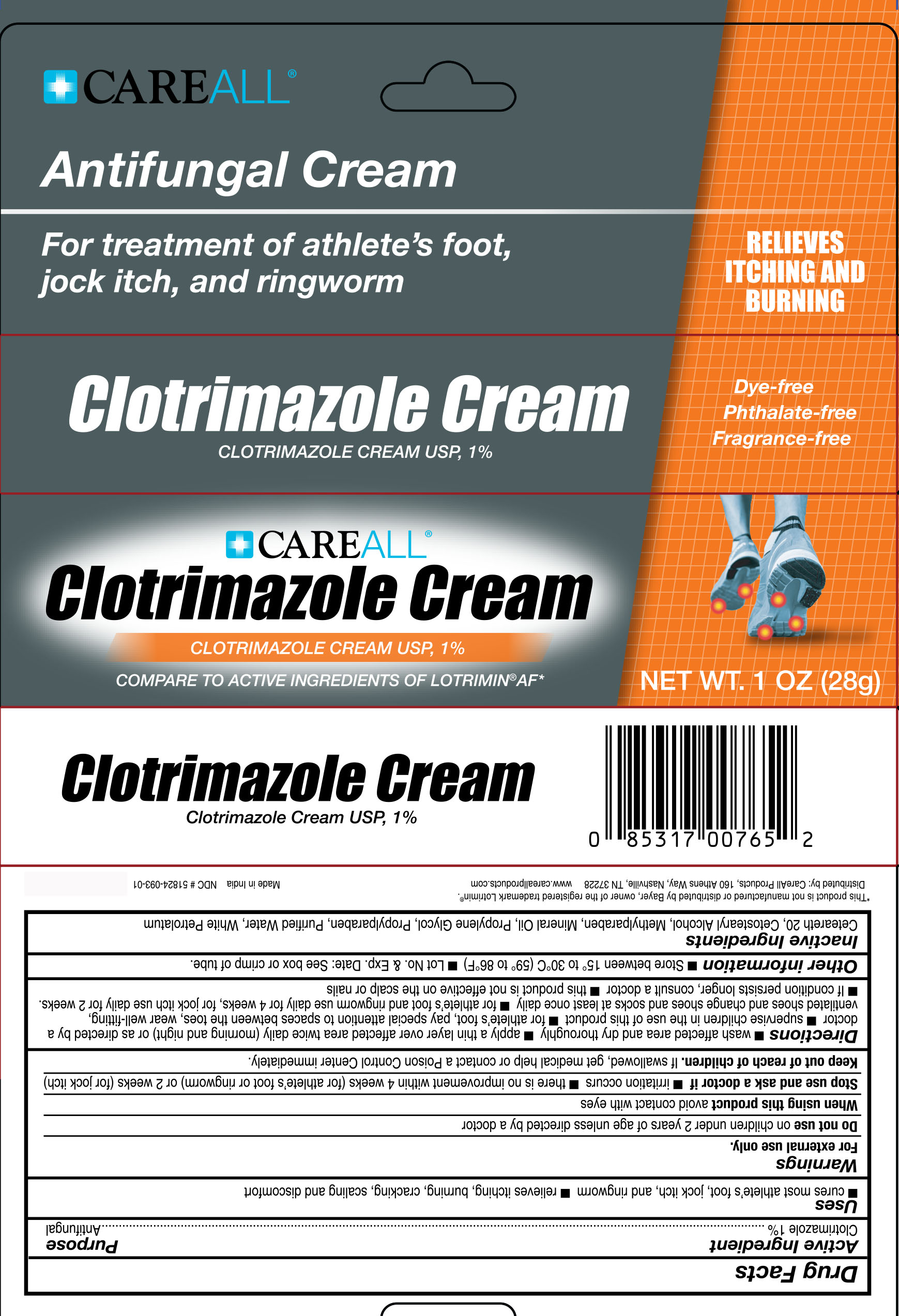 DRUG LABEL: CAREALL Clotrimazole
NDC: 51824-093 | Form: CREAM
Manufacturer: New World Imports, Inc
Category: otc | Type: HUMAN OTC DRUG LABEL
Date: 20251201

ACTIVE INGREDIENTS: CLOTRIMAZOLE 10 mg/1 g
INACTIVE INGREDIENTS: POLYOXYL 20 CETOSTEARYL ETHER; CETOSTEARYL ALCOHOL; MINERAL OIL; METHYLPARABEN; PROPYLPARABEN; WATER; WHITE PETROLATUM; PROPYLENE GLYCOL

Drug Facts

Active Ingredient

Clotrimazole 1%

Purpose

Antifungal

Keep out of reach of children. If swallowed, get medical help or contact a Poison Control Center immediately.

Uses

- Cures most athlete's foot, jock itch and ringworm.
- Relieves itching, burning, cracking, scaling, and discomfort

Warnings

For external use only.

Do not use onchildren under 2 years of age unless directed by a doctor.

When using this productavoid contact with eyes

Stop use and ask doctor if

- irritation occurs
- there is no improvement in 4 weeks (for athlete's foot or ringworm) or 2 weeks (for jock itch)

Directions

- wash affected area and dry thoroughly
- apply a thin layer over affected area twice daily (morning and night) or as directed by a doctor
- supervise children in the use of this product
- for athlete's foot, pay special attention to spaces between the toes, wear well-fitting, ventilated shoes and change shoes and socks at least once daily
- for atlete's foot and ringworm, use daily for 4 weeks; for jock itch, use daily for 2 weeks
- if condition persists longer, ask a doctor
- this product is not effective on the scalp or nails

Inactive Ingredients

Ceteareth 20, Cetostearyl Alcohol, Methylparaben, Mineral Oil, Propylene Glycol, Propylparaben, Purified Water, White Petrolatum